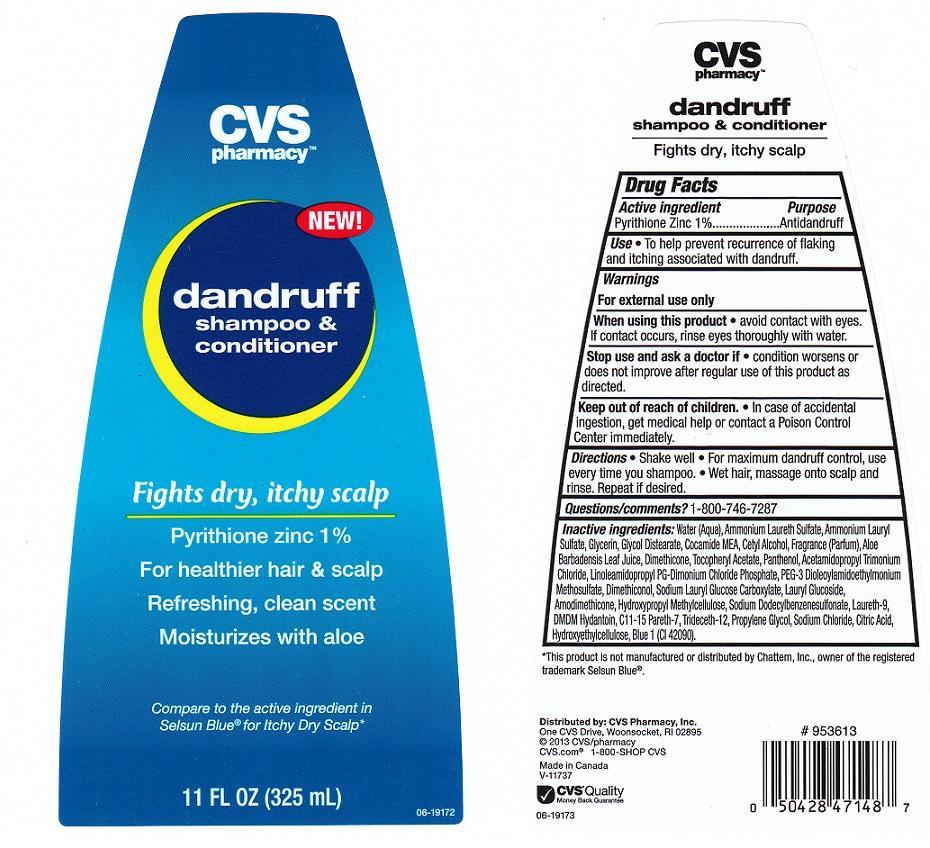 DRUG LABEL: CVS PHARMACY
NDC: 59779-428 | Form: LIQUID
Manufacturer: CVS PHARMACY
Category: otc | Type: HUMAN OTC DRUG LABEL
Date: 20131206

ACTIVE INGREDIENTS: PYRITHIONE ZINC 10 mg/1 mL
INACTIVE INGREDIENTS: WATER; AMMONIUM LAURETH-3 SULFATE; AMMONIUM LAURYL SULFATE; GLYCERIN; GLYCOL DISTEARATE; COCO MONOETHANOLAMIDE; CETYL ALCOHOL; ALOE VERA LEAF; DIMETHICONE; .ALPHA.-TOCOPHEROL ACETATE; PANTHENOL; ACETAMIDOPROPYL TRIMONIUM CHLORIDE; LINOLEAMIDOPROPYL PG-DIMONIUM CHLORIDE PHOSPHATE; PEG-3 DISTEAROYLAMIDOETHYLMONIUM METHOSULFATE; DIMETHICONOL (100000 CST); SODIUM LAURYL GLYCOL CARBOXYLATE; LAURYL GLUCOSIDE; AMODIMETHICONE (3500 CST); HYPROMELLOSES; SODIUM DODECYLBENZENESULFONATE; LAURETH-9; DMDM HYDANTOIN; C11-15 PARETH-7; TRIDECETH-12; PROPYLENE GLYCOL; SODIUM CHLORIDE; CITRIC ACID MONOHYDRATE; HYDROXYETHYL CELLULOSE (5000 CPS AT 1%); FD&C BLUE NO. 1

DRUG FACTS

ACTIVE INGREDIENT

PYRITHIONE ZINC 1%

PURPOSE

ANTIDANDRUFF

USES

TO HELP PREVENT RECURRENCE OF FLAKING AND ITCHING ASSOCIATED WITH DANDRUFF

WARNINGS

FOR EXTERNAL USE ONLY

WHEN USING THIS PRODUCT

AVOID CONTACT WITH EYES. IF CONTACT OCCURS, RINSE EYES THOROUGHLY WITH WATER

STOP USE AND ASK A DOCTOR IF

CONDITION WORSENS OR DOES NOT IMPROVE AFTER REGULAR USE OF THIS PRODUCT AS DIRECTED

KEEP OUT OF REACH OF CHILDREN

IN CASE OF ACCIDENTAL INGESTION, GET MEDICAL HELP OR CONTACT A POISON CONTROL CENTER IMMEDIATELY

DIRECTIONS

SHAKE WELL. FOR MAXIMUM DANDRUFF CONTROL, USE EVERY TIME YOU SHAMPOO. WET HAIR, MASSAGE ONTO SCALP AND RINSE. REPEAT IF DESIRED

QUESTIONS/COMMENTS?

1-800-746-7287

INACTIVE INGREDIENTS

WATER (AQUA), AMMONIUM LAURETH SULFATE, AMMONIUM LAURYL SULFATE, GLYCERIN, GLYCOL DISTEARATE, COCAMIDE MEA, CETYL ALCOHOL, FRAGRANCE (PARFUM), ALOE BARBADENSIS LEAF JUICE, DIMETHICONE, TOCOPHERYL ACETATE, PANTHENOL, ACETAMIDOPROPYL TRIMONIUM CHLORIDE, LINOLEAMIDOPROPYL PG-DIMONIUM CHLORIDE PHOSPHATE, PEG-3 DIOLEOYLAMIDOETHYLMONIUM METHOSULFATE, DIMETHICONOL, SODIUM LAURYL GLUCOSE CARBOXYLATE, LAURYL GLUCOSIDE, AMODIMETHICONE, HYDROXYPROPYL METHYLCELLULOSE, SODIUM DODECYLBENZENESULFONATE, LAURETH-9, DMDM HYDANTOIN, C11-15 PARETH-7, TRIDECETH-12, PROPYLENE GLYCOL, SODIUM CHLORIDE, CITRIC ACID, HYDROXYETHYLCELLULOSE, BLUE 1 (CI 42090)